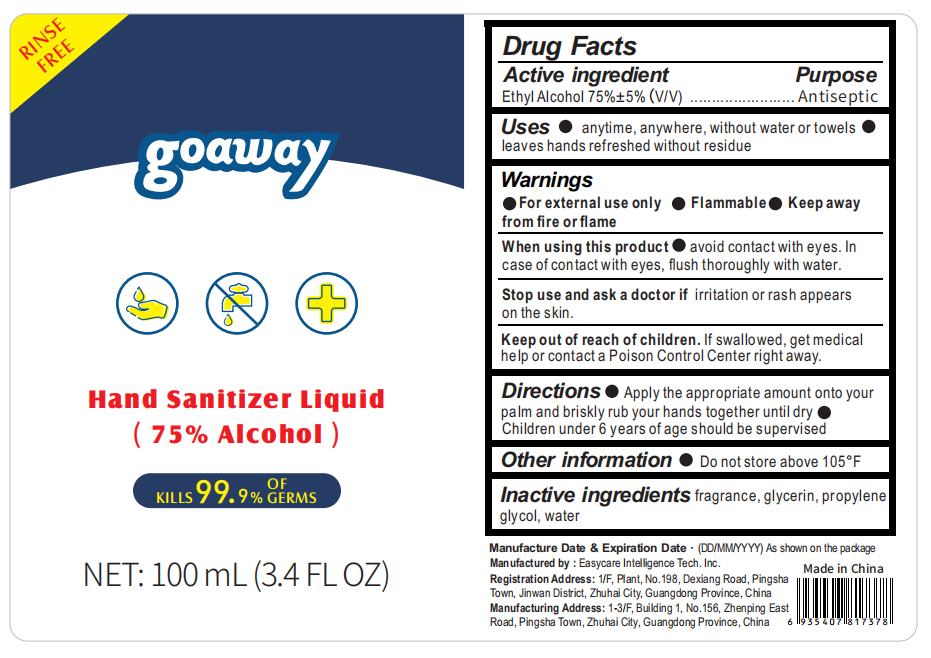 DRUG LABEL: Hand Sanitizer Liquid(75% Alcohol)
NDC: 56045-004 | Form: LIQUID
Manufacturer: Easycare Intelligence Tech. Inc.
Category: otc | Type: HUMAN OTC DRUG LABEL
Date: 20200420

ACTIVE INGREDIENTS: ALCOHOL 75 mL/100 mL
INACTIVE INGREDIENTS: GLYCERIN; PROPYLENE GLYCOL; WATER

When using this product●avoid contact with eyes. In case of contact with eyes, flush thoroughly with water.
Stop use and ask a doctor if irritation or rash appears on the skin.

INACTIVE INGREDIENT

fragrance, glycerin, propylene glycol, water

PURPOSE

Disinfection
Sterilization
No Rinseing

keep out of reach of children

ACTIVE INGREDIENT

alcohol

INDICATIONS AND USAGE

●Apply the appropriate amount onto your palm and briskly rub your hands together until dry

●Children under 6 years of age should be supervised

DOSAGE AND ADMINISTRATION

●For external use only ●Flammable:Keep away from fire or flame